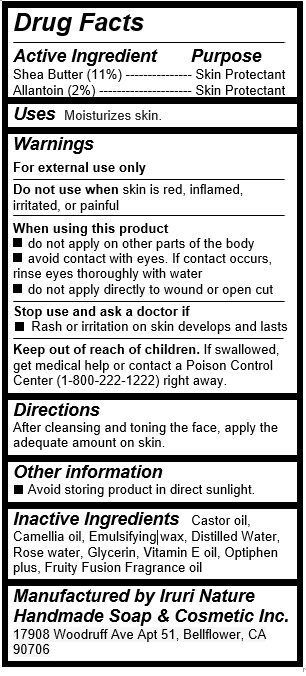 DRUG LABEL: Yellow
NDC: 71547-110 | Form: LOTION
Manufacturer: Iruri Nature Handmade Soap & Cosmetic Inc
Category: otc | Type: HUMAN OTC DRUG LABEL
Date: 20170725

ACTIVE INGREDIENTS: ALLANTOIN 0.4 g/20 mL; SHEA BUTTER 2.2 g/20 mL
INACTIVE INGREDIENTS: WATER; GLYCERIN; .ALPHA.-TOCOPHEROL; CAMELLIA OIL; CASTOR OIL

Yellow Lotion (Shea Butter)

Active Ingredients

Shea Butter (11%)

Allantoin (2%)

Purpose

Skin Protectant

Uses

Moisturizes skin

Warnings

For external use only

Do not use when skin is red, inflamed, irritated, or painful

When using this product

- do not apply on other parts of the body

- avoid contact with eyes. If contact occurs, rinse eyes thoroughly with water

- do not apply directly to wound or open cut

Stop use and ask a doctor if

- Rash or irritation on skin develops and lasts

Directions

After cleansing and toning the face, apply the adequate amount on skin.

Inactive Ingredients

Castor oil, Camellia oil, Emulsifying wax, Distilled Water, Rose water, Glycerin, Vitamin E oil, Optiphen plus, Fruity Fusion Fragrance oil

Keep out of reach of children

If swallowed, get medical help or contact a Poison Control Center (1-800-222-1222) right away.